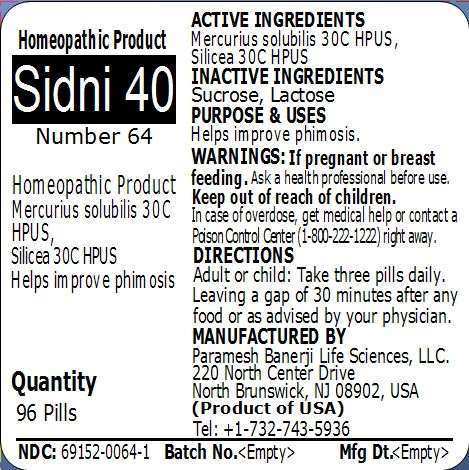 DRUG LABEL: Sidni 40 (Number 64)
NDC: 69152-0064 | Form: PELLET
Manufacturer: Paramesh Banerji Life Sciences LLC
Category: homeopathic | Type: HUMAN OTC DRUG LABEL
Date: 20150227

ACTIVE INGREDIENTS: MERCURIUS SOLUBILIS 30 [hp_C]/1 1; SILICON DIOXIDE 30 [hp_C]/1 1
INACTIVE INGREDIENTS: SUCROSE; LACTOSE

Active Ingredients

Mercurius solubilis 30C HPUS, Silicea 30C HPUS

Inactive Ingredients

Sucrose, Lactose

Purpose

Helps improve phimosis

Uses

Helps improve phimosis

Warnings

If pregnant or breast feeding ask a health professional before use.

Keep out of reach of children. In case of overdose, get medical help or contact a Poison Control Center (1-800-222-1222) right away.

Direction

Adult or child: Take three pills daily. Leaving a gap of 30 minutes after any food or as advised by your physician.

Manufactured by

Paramesh Banerji Life Sciences, LLC

220 North Center Drive

North Brunswick, NJ 08902, USA

Product of USA

Tel: +1-732-743-5936

Principal Display Panel

Homeopathic Product

Sidni 40

Number 64

Homeopathic Product

Mercurius solubilis 30C HPUS, Silicea 30C HPUS

Helps improve phimosis

Quantity

96 Pills